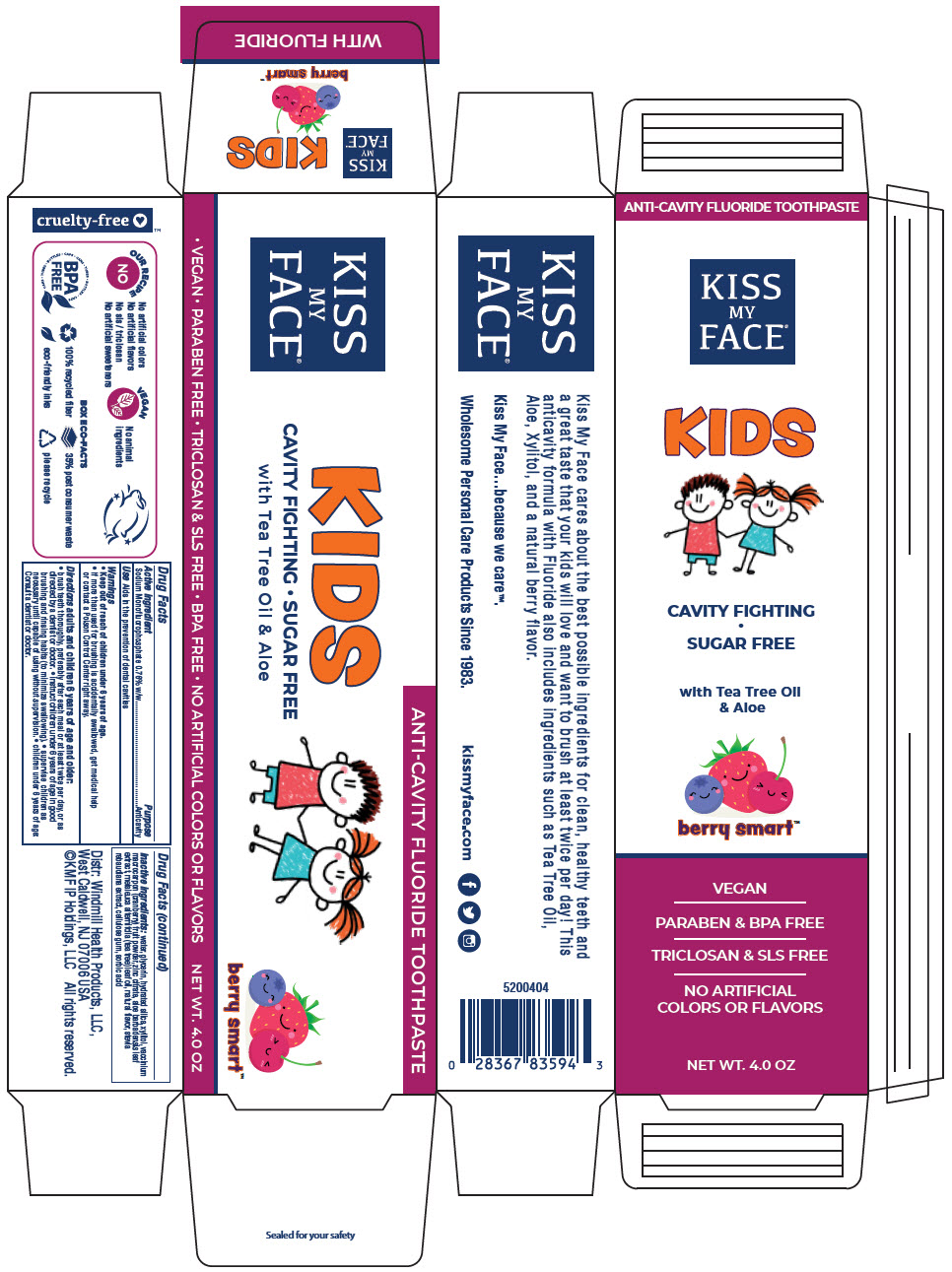 DRUG LABEL: Kiss My Face Kids Fluoride - Berry Smart
NDC: 74154-014 | Form: PASTE, DENTIFRICE
Manufacturer: Windmill Health Products, LLC
Category: otc | Type: HUMAN OTC DRUG LABEL
Date: 20220208

ACTIVE INGREDIENTS: Sodium Monofluorophosphate 7.6 mg/1 g
INACTIVE INGREDIENTS: water; glycerin; hydrated silica; xylitol; cranberry; zinc citrate; aloe vera leaf; tea tree oil; STEVIA REBAUDIUNA LEAF; CARBOXYMETHYLCELLULOSE SODIUM, UNSPECIFIED; sorbic acid

Kiss My Face® Kids Fluoride Toothpaste - Berry Smart™

Drug Facts

Active ingredient

Sodium Monofluorophosphate 0.76% w/w

Purpose

Anticavity

Use

Aids in the prevention of dental cavities

Warnings

- Keep out of reach of children under 6 years of age.
- If more than used for brushing is accidentally swallowed, get medical help or contact a Poison Control Center right away.

Directions

adults and children 6 years of age and older:

- brush teeth thoroughly, preferably after each meal or at least twice per day, or as directed by a dentist or doctor.
- instruct children under 6 years of age in good brushing and rinsing habits (to minimize swallowing).
- supervise children as necessary until capable of using without supervision.
- children under 6 years of age: Consult a dentist or doctor.

Inactive ingredients:

water, glycerin, hydrated silica, xylitol, vaccinium macrocarpon (cranberry) fruit powder, zinc citrate, aloe barbadensis leaf extract, melaleuca alternifolia (tea tree) leaf oil, natural flavor, stevia rebaudiana extract, cellulose gum, sorbic acid

PRINCIPAL DISPLAY PANEL - 4.0 OZ Tube Carton

ANTI-CAVITY FLUORIDE TOOTHPASTE

KISS
MY
FACE®

KIDS

CAVITY FIGHTING

SUGAR FREE

with Tea Tree Oil
& Aloe

berry smart™

VEGAN

PARABEN & BPA FREE

TRICLOSAN & SLS FREE

NO ARTIFICIAL
COLORS OR FLAVORS

NET WT. 4.0 OZ